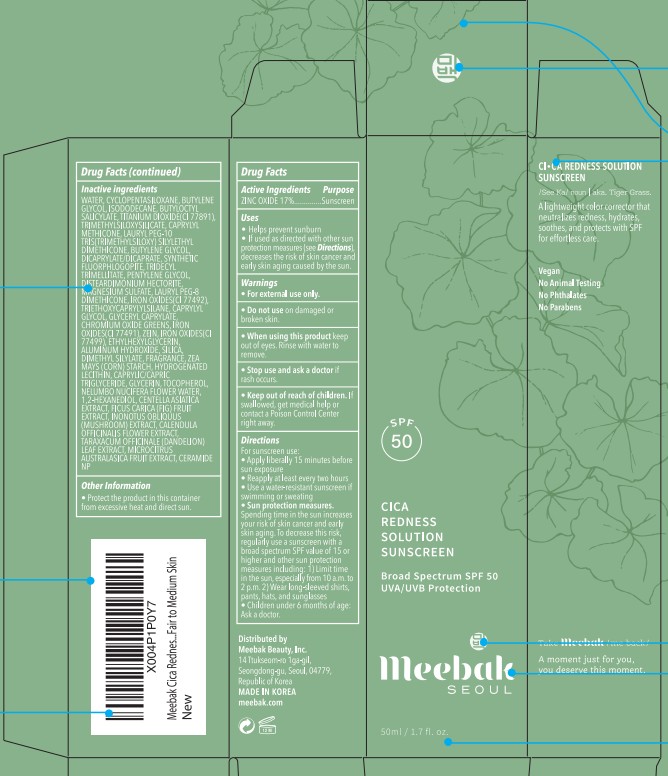 DRUG LABEL: Cica Redness Solution Sunscreen
NDC: 73877-006 | Form: CREAM
Manufacturer: Meebak Beauty, Inc
Category: otc | Type: HUMAN OTC DRUG LABEL
Date: 20250818

ACTIVE INGREDIENTS: ZINC OXIDE 170 mg/1 mL
INACTIVE INGREDIENTS: WATER; CYCLOPENTASILOXANE; BUTYLENE GLYCOL; ISODODECANE; BUTYLOCTYL SALICYLATE; TITANIUM DIOXIDE; TRIMETHYLSILOXYSILICATE (M/Q 0.6-0.8); CAPRYLYL TRISILOXANE; BUTYLENE GLYCOL DICAPRYLATE/DICAPRATE; MAGNESIUM POTASSIUM ALUMINOSILICATE FLUORIDE; TRIDECYL TRIMELLITATE; PENTYLENE GLYCOL; DISTEARDIMONIUM HECTORITE; MAGNESIUM SULFATE, UNSPECIFIED FORM; LAURYL PEG-8 DIMETHICONE (300 CPS); FERRIC OXIDE YELLOW; TRIETHOXYCAPRYLYLSILANE; CAPRYLYL GLYCOL; GLYCERYL MONOCAPRYLATE; CHROMIC OXIDE; FERRIC OXIDE RED; ZEIN; FERROSOFERRIC OXIDE; ETHYLHEXYLGLYCERIN; ALUMINUM HYDROXIDE; SILICA DIMETHYL SILYLATE; STARCH, CORN; HYDROGENATED SOYBEAN LECITHIN; MEDIUM-CHAIN TRIGLYCERIDES; GLYCERIN; TOCOPHEROL; NELUMBO NUCIFERA FLOWER OIL; 1,2-HEXANEDIOL; CENTELLA ASIATICA TRITERPENOIDS; FIG; INONOTUS OBLIQUUS FRUITING BODY; CALENDULA OFFICINALIS FLOWER; TARAXACUM OFFICINALE LEAF; CITRUS AUSTRALASICA WHOLE; CERAMIDE NP

73877-006_CICA REDNESS SOLUTION SUNSCREEN

ACTIVE INGREDIENT

Zinc Oxide 17%

PURPOSE

Sunscreen

INDICATIONS AND USAGE

Helps prevent sunburn

If used as directed with other sun protection measures (see Directions), decreases the risk of skin cancer and early skin aging caused by the sun.

DOSAGE AND ADMINISTRATION

For sunscreen use:
- Apply liberally 15 minutes before sun exposure
- Reapply at least every two hours
- Use a water-resistant sunscreen if swimming or sweating
- Sun protection measures. Spending time in the sun increases your risk of skin cancer and early skin aging. To decrease this risk, regularly use a sunscreen with a broad spectrum SPF value of 15 or higher and other sun protection measures including: 1) Limit time in the sun, especially from 10 a.m. to 2 p.m. 2) Wear long-sleeved shirts, pants, hats, and sunglasses
- Children under 6 months of age: Ask a doctor.

WARNINGS

For external use only

Do not use on damaged or broken skin.

When using this product keep out of eyes. Rinse with water to remove.

Stop use and ask a doctor if rash occurs.

Keep out of reach of children.

If swallowed, get medical help or contact a Poison Control Center right away.

INACTIVE INGREDIENT

WATER, CYCLOPENTASILOXANE, BUTYLENE GLYCOL, ISODODECANE, BUTYLOCTYL SALICYLATE, TITANIUM DIOXIDE (CI 77891), TRIMETHYLSILOXYSILICATE, CAPRYLYL METHICONE, LAURYL PEG-10 TRIS(TRIMETHYLSILOXY) SILYLETHYL DIMETHICONE, BUTYLENE GLYCOL, DICAPRYLATE/DICAPRATE, SYNTHETIC FLUORPHLOGOPITE, TRIDECYL TRIMELLITATE, PENTYLENE GLYCOL, DISTEARDIMONIUM HECTORITE, MAGNESIUM SULFATE, LAURYL PEG-8 DIMETHICONE, IRON OXIDES(CI 77492), TRIETHOXYCAPRYLYLSILANE, CAPRYLYL GLYCOL, GLYCERYL CAPRYLATE, CHROMIUM OXIDE GREENS, IRON OXIDES(CI 77491), ZEIN, IRON OXIDES(CI 77499), ETHYLHEXYLGLYCERIN, ALUMINUM HYDROXIDE, SILICA, DIMETHYL SILYLATE, FRAGRANCE, ZEA MAYS (CORN) STARCH, HYDROGENATED LECITHIN, CAPRYLIC/CAPRIC TRIGLYCERIDE, GLYCERIN, TOCOPHEROL, NELUMBO NUCIFERA FLOWER WATER, 1,2-HEXANEDIOL, CENTELLA ASIATICA EXTRACT, FICUS CARICA (FIG) FRUIT EXTRACT, INONOTUS OBLIQUUS (MUSHROOM) EXTRACT, CALENDULA OFFICINALIS FLOWER EXTRACT, TARAXACUM OFFICINALE (DANDELION) LEAF EXTRACT, MICROCITRUS AUSTRALASICA FRUIT EXTRACT, CERAMIDE NP

OTHER SAFETY INFORMATION

Protect the product in this container from excessive heat and direct sun